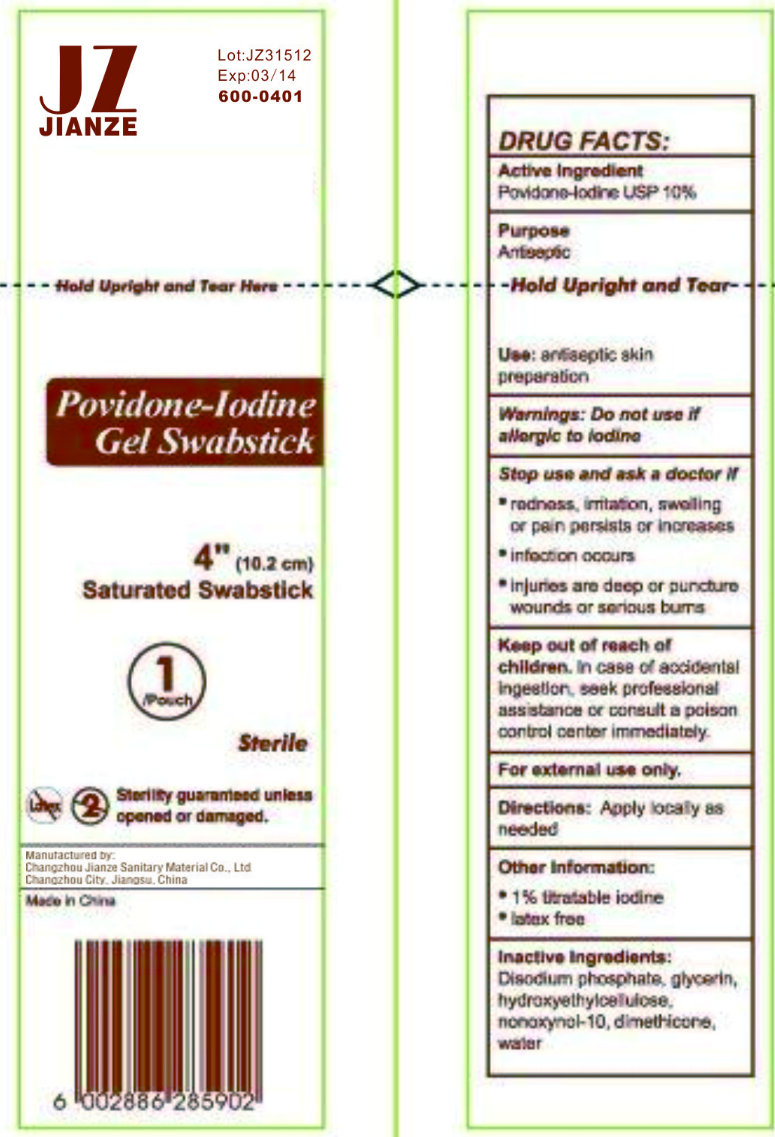 DRUG LABEL: JIANZE POVIDONE-IODINE
NDC: 50666-005 | Form: GEL
Manufacturer: Changzhou Jianze Sanitary Material Co., Ltd.
Category: otc | Type: HUMAN OTC DRUG LABEL
Date: 20120620

ACTIVE INGREDIENTS: POVIDONE-IODINE 10 g/100 g
INACTIVE INGREDIENTS: SODIUM PHOSPHATE, DIBASIC, ANHYDROUS; GLYCERIN; NONOXYNOL-10; DIMETHICONE; WATER

JIANZE POVIDONE-IODINE GEL SWABSTICK

ACTIVE INGREDIENT

Povidone-Iodine USP 10%

PURPOSE

Antiseptic

USE:

Antiseptic skin preparation

WARNINGS:

Do not use if allergic to Iodine.

STOP USE AND ASK A DOCTOR IF:

- redness, irritation, swelling or pain persists or increases
- infection occurs
- injuries are deep or puncture wounds or serious burns

KEEP OUT OF REACH OF CHILDREN.

In case of accidental ingestion, seek professional assistance or consult a poison control center immediately.

For External Use Only.

DIRECTIONS

Apply locally as needed.

OTHER INFORMATION

- 1% titratable iodine
- latex free

INACTIVE INGREDIENTS:

Disodium phosphate, glycerin, hydroxyethylcellulose, nonoxynol-10, dimethicone, water.